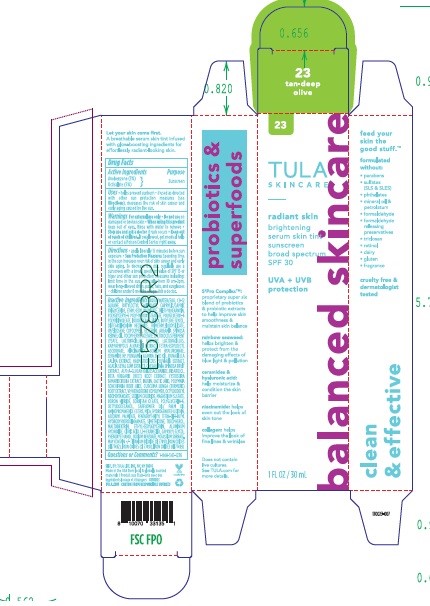 DRUG LABEL: TULA RADIANT SKIN BRIGHTENING SERUM SKIN TINT SUNSCREEN BROAD SPECTRUM SPF 30
NDC: 59735-207 | Form: LOTION
Manufacturer: MANA PRODUCTS, INC
Category: otc | Type: HUMAN OTC DRUG LABEL
Date: 20240103

ACTIVE INGREDIENTS: OCTISALATE 5 g/30 mL; AVOBENZONE 3 g/30 mL
INACTIVE INGREDIENTS: SAFFLOWER; TRIMETHYLSILOXYSILICATE (M/Q 0.6-0.8); ANHYDROUS CITRIC ACID; VINYLPYRROLIDONE/HEXADECENE COPOLYMER; MALTODEXTRIN; BORON NITRIDE; 1,2-HEXANEDIOL; ASCORBYL PALMITATE; ACACIA SEYAL WHOLE; HAEMATOCOCCUS PLUVIALIS; ISODODECANE; .ALPHA.-TOCOPHEROL ACETATE; FERRIC OXIDE RED; PHENOXYETHANOL; POLYGLYCERYL-6 POLYRICINOLEATE; KAPPAPHYCUS ALVAREZII; LECITHIN, SUNFLOWER; TOCOPHEROL; ETHYLHEXYL PALMITATE; FERROSOFERRIC OXIDE; GLYCERIN; OCTYLDODECYL NEOPENTANOATE; LACTOBACILLUS ACIDOPHILUS; DIMETHICONE; NIACINAMIDE; OCTYLDODECANOL; TURMERIC; CYSTOSEIRA TAMARISCIFOLIA; VINYLPYRROLIDONE/EICOSENE COPOLYMER; TETRAHEXYLDECYL ASCORBATE; POLYGLYCERIN-6; MICA; ALUMINUM HYDROXIDE; CAPRYLYL GLYCOL; .ALPHA.-BISABOLOL, (+)-; CAESALPINIA SPINOSA FRUIT POD; SMALLANTHUS SONCHIFOLIUS ROOT JUICE; LACTIC ACID; POTASSIUM SORBATE; ARGAN OIL; BETA VULGARIS; SILICON DIOXIDE; INULIN; CERAMIDE NP; HYALURONATE SODIUM; DUNALIELLA SALINA; CAPRYLIC/CAPRIC MONO/DI-GLYCERIDES; TITANIUM DIOXIDE; DISTEARDIMONIUM HECTORITE; PENTAERYTHRITOL 3,5-DI-TERT-BUTYL-4-HYDROXYHYDROCINNAMATE; BUTYLOCTYL SALICYLATE; LACTOCOCCUS LACTIS; .ALPHA.-GLUCAN OLIGOSACCHARIDE; KARUM SEED OIL; SODIUM BENZOATE; WATER; TRIETHYLHEXANOIN; SORBITAN; ETHYLHEXYLGLYCERIN; FERRIC OXIDE YELLOW; MAGNESIUM SULFATE ANHYDROUS; SODIUM CHLORIDE

TULA RADIANT SKIN BRIGHTENING SERUM SKIN TINT SUNSCREEN BROAD SPECTRUM SPF 30

Active Ingredients

Avobenzone 3%

Octisalate 5%

Purpose

Sunscreen

Uses

Helps prevent sunburn • if used as directed with other sun protection measures (see Directions), decreases the risk of skin cancer and early skin aging caused by the sun

Warnings

For external use only. Do not use on damaged or broken skin When using this product keep out of eyes. Rinse with water to remove.

Keep out of reach of children. If swallowed, get medical help or contact a Poison Control Center right away.

Directions

Apply liberally 15 minutes before sun exposure. Sun Protection Measures. Spending time in the sun increases your risk of skin cancer and early skin aging. To decrease this risk, regularly use a sunscreen with a Broad Spectrum SPF of 15 or higher and other sun protection measures including: limit time in the sun, especially from 10 am – 2 pm, wear long sleeved shirts, pants, hats and sunglasses. Children under 6 months: Ask a doctor

Inactive Ingredients

Aqua/Water/Eau, C9-12 Alkane , Butyloctyl Salicylate, Caprylic/Capric Triglyceride, Ethylhexyl Palmitate, Triethylhexanoin, Polyglyceryl-6 Polyhydroxystearate, Polyglyceryl-6 Polyricinoleate, Isododecane, Silica, Butylene Glycol, Disteardimonium Hectorite, Trimethylsiloxysilicate, VP/Eicosene Copolymer, Glycerin, Argania Spinosa Kernel Oil, Tocopheryl Acetate, VP/Hexadecene Copolymer, Octyldodecyl Neopentanoate, Sodium Chloride, Magnesium Sulfate, Boron Nitride, Sorbitan Oleate, Polyglycerin-6, Caesalpinia Spinosa Fruit Extract, Octyldodecanol, Safflower oil/ Palm oil aminopropanediol esters , Mica , Lactococcus Ferment Lysate, Alpha-Glucan Oligosaccharide, Hydrogenated Lecithin, Bisabolol, Pentaerythrityl Tetra-di-t-butyl Hydroxyhydrocinnamate, Simethicone, Kappaphycus Alvarezii Extract, Pongamia Glabra Seed Oil , Beta Vulgaris (Beet) Root Extract, Cystoseira Tamariscifolia Extract, Inulin, Niacinamide, Tocopherol, Tetrahexyldecyl Ascorbate, Ascorbyl Palmitate, Lactic Acid, Polymnia Sonchifolia Root Juice, Lactobacillus Ferment, Curcuma Longa (Turmeric) Root Extract, Maltodextrin, Ceramide NP, Dunaliella Salina Extract , Haematococcus Pluvialis Extract , Acacia Seyal Gum Extract, Lactobacillus, Ethylhexylglycerin, Aluminum Hydroxide, Sodium Hyaluronate, Citric Acid, 1,2-Hexanediol, Caprylyl Glycol, Phenoxyethanol, Sodium Benzoate, Potassium Sorbate, Titanium Dioxide (CI 77891), Iron Oxides (CI 77492), Iron Oxides (CI 77491), Iron Oxides (CI 77499).

Stop use and ask a doctor if rash occurs.

RECENT MAJOR CHANGES

Dosage & Admin update